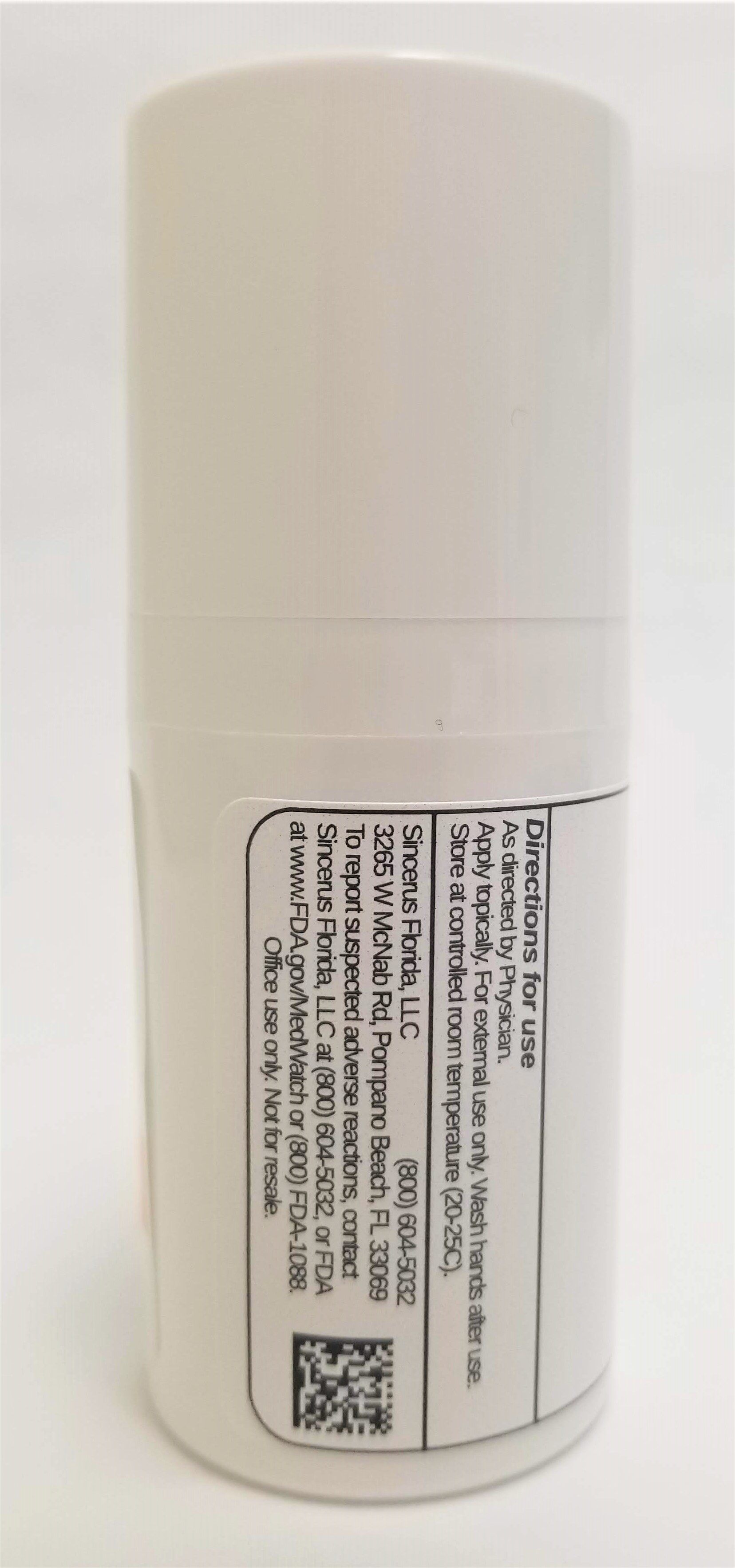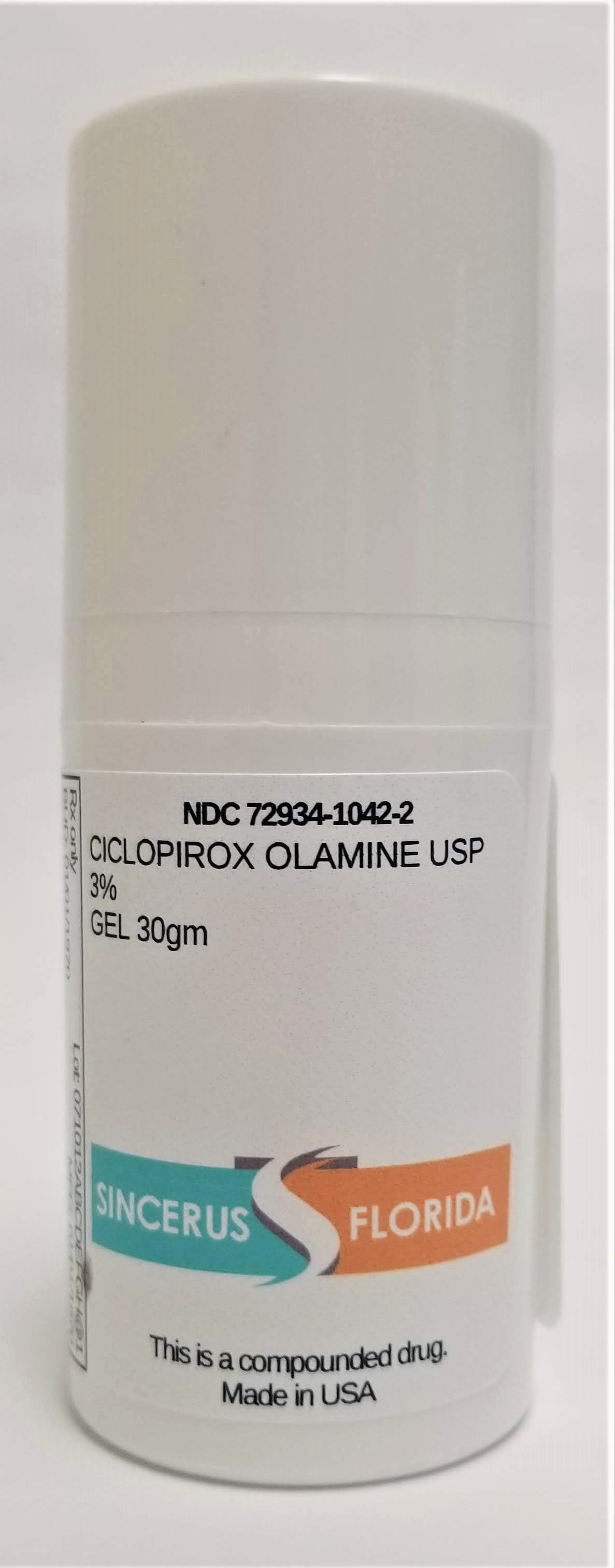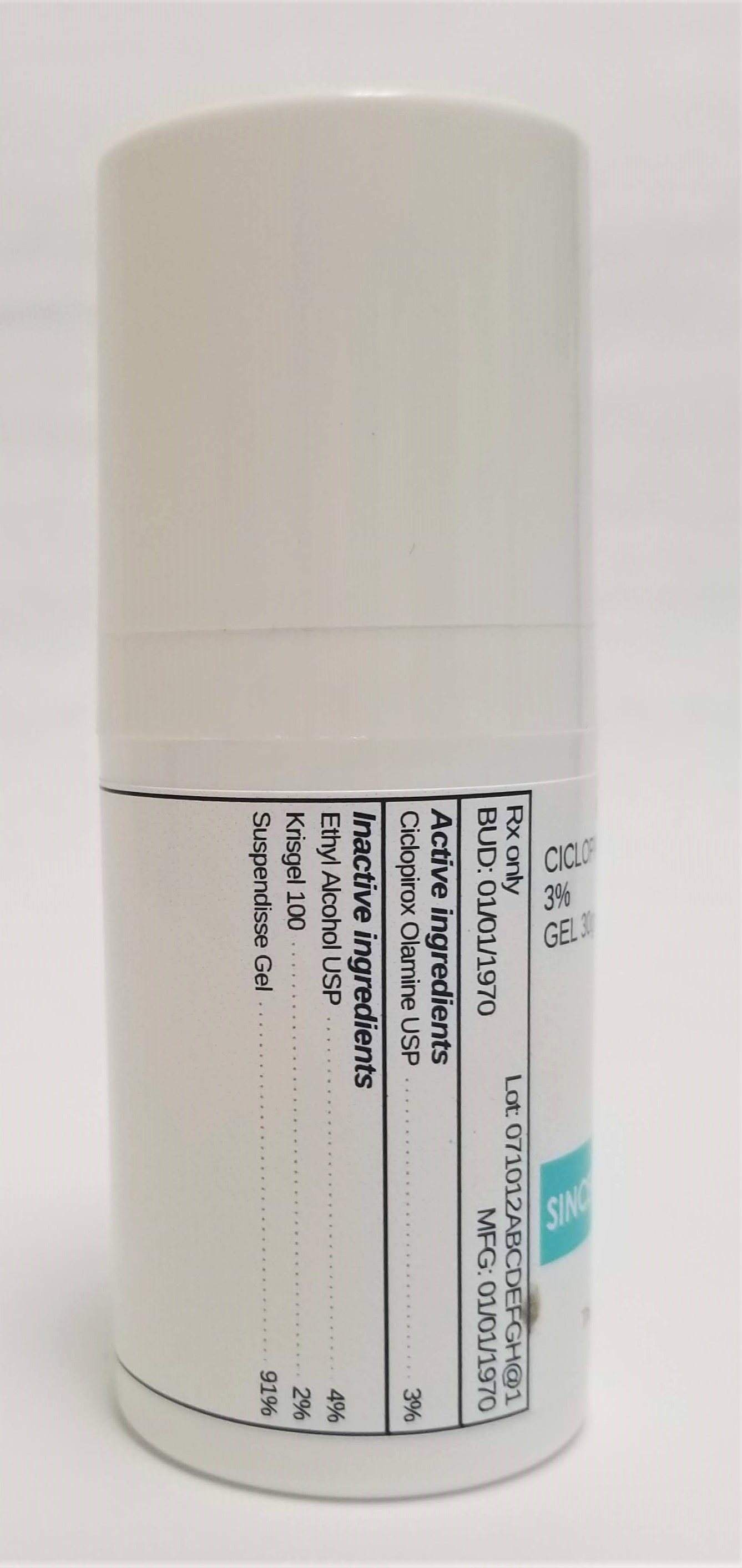 DRUG LABEL: CICLOPIROX 3%
NDC: 72934-1042 | Form: GEL
Manufacturer: Sincerus Florida, LLC
Category: prescription | Type: HUMAN PRESCRIPTION DRUG LABEL
Date: 20190520

ACTIVE INGREDIENTS: CICLOPIROX OLAMINE 3 g/100 g

CICLOPIROX 3%